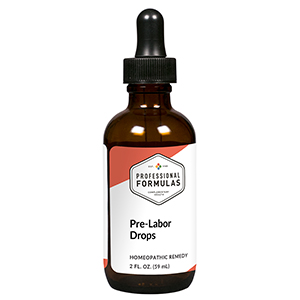 DRUG LABEL: Pre-Labor Drops
NDC: 63083-2137 | Form: LIQUID
Manufacturer: Professional Complementary Health Formulas
Category: homeopathic | Type: HUMAN OTC DRUG LABEL
Date: 20190815

ACTIVE INGREDIENTS: ARNICA MONTANA WHOLE 5 [hp_X]/59 mL; CAULOPHYLLUM THALICTROIDES ROOT 5 [hp_X]/59 mL; BLACK COHOSH 5 [hp_X]/59 mL; GELSEMIUM SEMPERVIRENS ROOT 5 [hp_X]/59 mL; PULSATILLA MONTANA WHOLE 5 [hp_X]/59 mL
INACTIVE INGREDIENTS: ALCOHOL; WATER

C137

ACTIVE INGREDIENTS

Arnica montana 5C
Caulophyllum thalictroides 5C
Cimicifuga racemosa 5C
Gelsemium sempervirens 5C
Pulsatilla 5C

QUESTIONS

Professional Formulas

PO Box 2034 Lake Oswego, OR 97035

INDICATIONS

For the temporary relief of occasional headache, minor backache, swelling or aches in legs, or fatigue that is common during pregnancy.*

PURPOSE

*Claims based on traditional homeopathic practice, not accepted medical evidence. Not FDA evaluated.

WARNINGS

In case of overdose, get medical help or contact a poison control center right away.

Keep out of the reach of children.

PREGNANCY OR BREAST FEEDING

If pregnant or breastfeeding, ask a healthcare professional before use.

DIRECTIONS

Place drops under tongue 30 minutes before/after meals. Adults and children 12 years and over: Take 10 drops up to 3 times per day. Consult a physician for use in children under 12 years of age. Not intended for use in infants.

OTHER INFORMATION

Tamper resistant. If seal is broken, do not use. After opening, close container tightly and store at room temperature away from heat.

INACTIVE INGREDIENTS

10% ethanol, purified water, 8% vegetable glycerin (from soy).

LABEL

Est 1985

Professional Formulas

Complementary Health

Pre-Labor Drops

Homeopathic Remedy

2 FL. OZ. (59 mL)